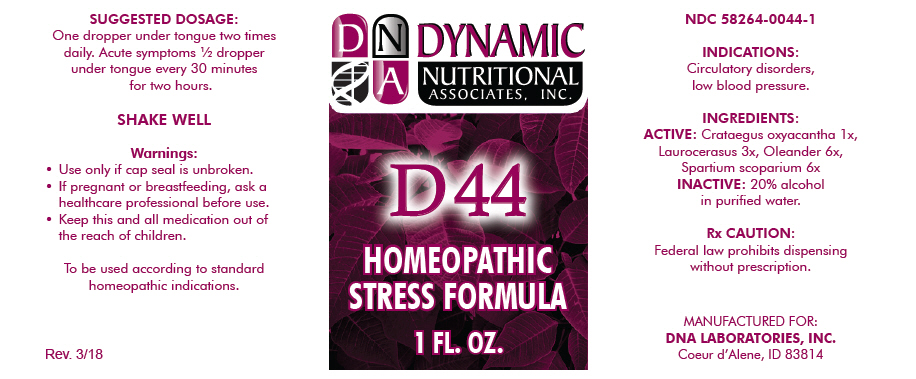 DRUG LABEL: D-44
NDC: 58264-0044 | Form: SOLUTION
Manufacturer: DNA Labs, Inc.
Category: homeopathic | Type: HUMAN OTC DRUG LABEL
Date: 20250113

ACTIVE INGREDIENTS: CRATAEGUS LAEVIGATA FRUIT 1 [hp_X]/1 mL; PRUNUS LAUROCERASUS LEAF 3 [hp_X]/1 mL; NERIUM OLEANDER LEAF 6 [hp_X]/1 mL; CYTISUS SCOPARIUS WHOLE 6 [hp_X]/1 mL
INACTIVE INGREDIENTS: ALCOHOL; WATER

D-44

NDC 58264-0044-1

INDICATIONS

PURPOSE

Circulatory disorders, low blood pressure.

INGREDIENTS

ACTIVE

Crataegus oxyacantha 1x, Laurocerasus 3x, Oleander 6x, Spartium scoparium 6x

INACTIVE

20% alcohol in purified water.

Rx CAUTION

Federal law prohibits dispensing without prescription.

SUGGESTED DOSAGE

One dropper under tongue two times daily. Acute symptoms ½ dropper under tongue every 30 minutes for two hours.

STORAGE AND HANDLING

SHAKE WELL

Warnings

- Use only if cap seal is unbroken.

PREGNANCY OR BREAST FEEDING

- If pregnant or breastfeeding, ask a healthcare professional before use.

KEEP OUT OF REACH OF CHILDREN

- Keep this and all medication out of the reach of children.

To be used according to standard homeopathic indications.

PRINCIPAL DISPLAY PANEL - 1 FL. OZ. Bottle Label

DYNAMIC
NUTRITIONAL
ASSOCIATES, INC.

D 44

HOMEOPATHIC
STRESS FORMULA

1 FL. OZ.